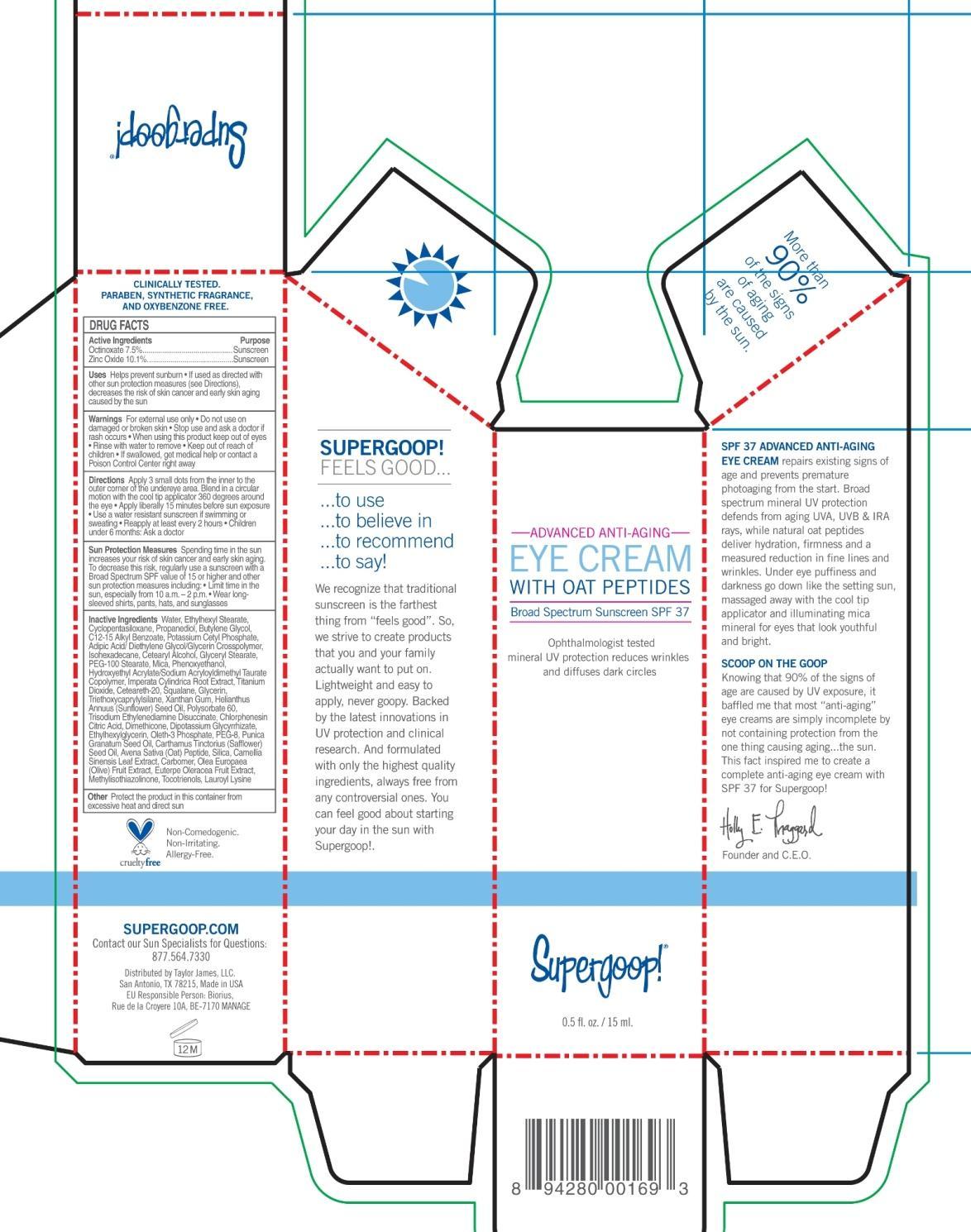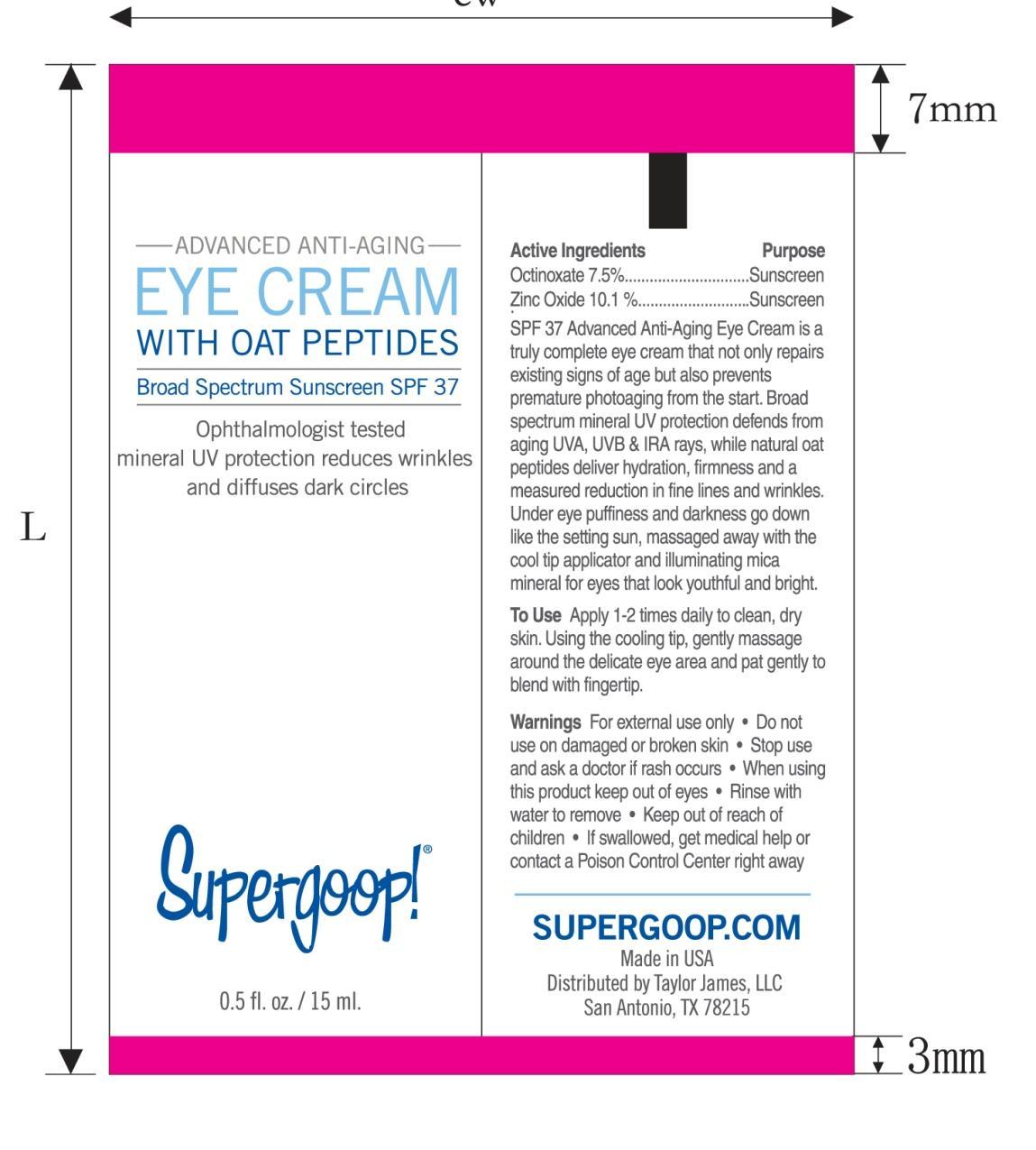 DRUG LABEL: Advanced Anti-Aging Eye Broad Spectrum SPF 37

NDC: 75936-120 | Form: CREAM
Manufacturer: TAYLOR JAMES, LTD.
Category: otc | Type: HUMAN OTC DRUG LABEL
Date: 20201112

ACTIVE INGREDIENTS: OCTINOXATE 75 mg/1 mL; ZINC OXIDE 10.1 mg/1 mL
INACTIVE INGREDIENTS: WATER; ETHYLHEXYL STEARATE; CYCLOMETHICONE 5; PROPANEDIOL; BUTYLENE GLYCOL; ALKYL (C12-15) BENZOATE; POTASSIUM CETYL PHOSPHATE; ISOHEXADECANE; CETOSTEARYL ALCOHOL; GLYCERYL MONOSTEARATE; PEG-100 STEARATE; MICA; PHENOXYETHANOL; HYDROXYETHYL ACRYLATE/SODIUM ACRYLOYLDIMETHYL TAURATE COPOLYMER (45000 MPA.S AT 1%); IMPERATA CYLINDRICA ROOT; TITANIUM DIOXIDE; POLYOXYL 20 CETOSTEARYL ETHER; SQUALANE; GLYCERIN; TRIETHOXYCAPRYLYLSILANE; XANTHAN GUM; SUNFLOWER OIL; POLYSORBATE 60; TRISODIUM ETHYLENEDIAMINE DISUCCINATE; CHLORPHENESIN; CITRIC ACID MONOHYDRATE; DIMETHICONE; GLYCYRRHIZINATE DIPOTASSIUM; ETHYLHEXYLGLYCERIN; OLETH-3 PHOSPHATE; POLYETHYLENE GLYCOL 400; PUNICA GRANATUM SEED OIL; SAFFLOWER OIL; SILICON DIOXIDE; GREEN TEA LEAF; CARBOMER HOMOPOLYMER TYPE C (ALLYL PENTAERYTHRITOL CROSSLINKED); BLACK OLIVE; METHYLISOTHIAZOLINONE; TOCOTRIENOLS; LAUROYL LYSINE

Advanced Anti-Aging Eye Cream

Active Ingredients Purpose

Octinoxate 7.5% Sunscreen

Zinc Oxide 10.1% Sunscreen

PURPOSE

Uses Helps Prevent Sunburn

If used as directed with other sun protection measures (see Directions), decreases the risk of skin cancer and early skin aging caused by the sun

Keep out of reach of children. If swallowed, get medical help or contact a Poison Control Center right away.

Stop use and ask a doctor if rash occurs

Warnings

For external use only

Do not use on damaged or broken skin.

When using this product keep out of eye. Rinse with water to remove.

DOSAGE AND ADMINISTRATION

Directions Apply Liberally 15 minutes before sun exposure

Use a water resistant if swimming or sweating

Reapply at least every 2 hours

Children under 6 months: Ask a doctor

Sun Protection Measures

Spending time in the sun increases your risk of early skin cancer and early skin aging. To decrease this risk, regularly use a sunscreen with a Broad Spectrum SPF calue of 15 or higher and other sun protection measures including:

Limit time in the sun, especially from 10 a.m.-2p.m.

Wear long-sleeved shirts, pants, hats, and sunglasses

INACTIVE INGREDIENT

Water, Ethylhexyl Stearate, Cyclopentasiloxane, Propanediol, Butylene Glycol, C12-15 Alkyl Benzoate, Potassium Cetyl Phosphate, Adipic Acid/Diethylene Glycol/Glycerin Crosspolymer, Isohexadecane, Cetearyl Alcohol, Glyceryl Stearate, PEG-100 Stearate, Mica, Phenoxyethanol, Hydroxyethyl Acrylate/Sodium Acryloyldimethyl Taurate Copolymer, Imperata Cylindrica Root Extract, Titanium Dioxide, Ceteareth-20, Squalane, Glycerin, Triethoxycaprylylsilane, Xanthan Gum, Helianthus Annuus (Sunflower) Seed Oil, Polysorbate 60, Trisodium Ethylene Disuccinate, Chlorphenesin, Citric Acid, Dimethicone, Dipotassium Glycyrrhizate, Ethylhexylglycerin, Oleth-3 Phosphate, PEG-8, Punica Granatum Seed Oil, Avena Sativa (Oat) Peptide, Silica, Camellia Sinensis Leaf Extract, Carbomer, Olea Europaea (Olive) Fruit Extract, Euterpe Oleracea Fruit Extract, Methylisothiazolinone, Tocotrienols, Lauroyl Lysine.

PACKAGE LABEL

Advanced Anti-Aging Eye Cream Broad Spectrum SPF 37

Wrinkle-reducing oat peptide complex

Supergoop!

Opthamologist tested for sensitive eye area.

0.5 fl. oz./15 ml.